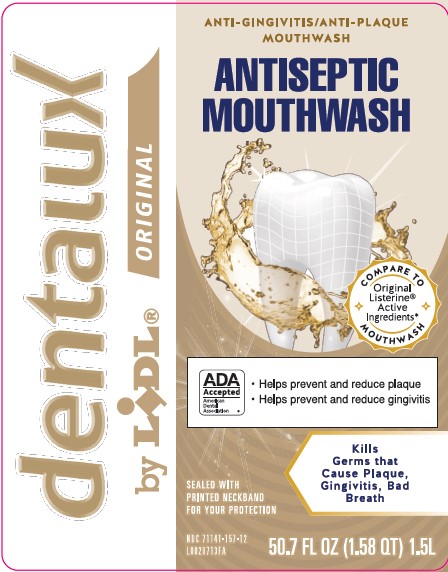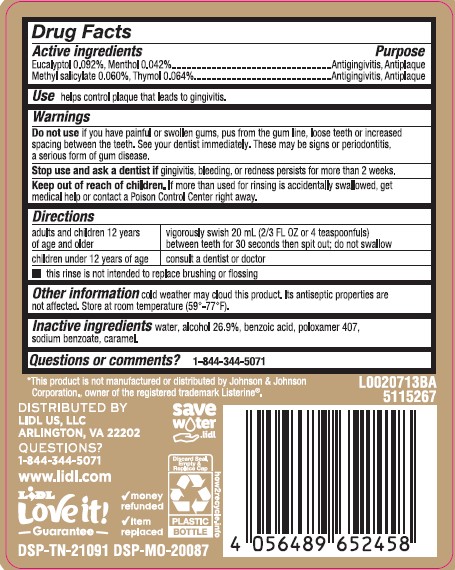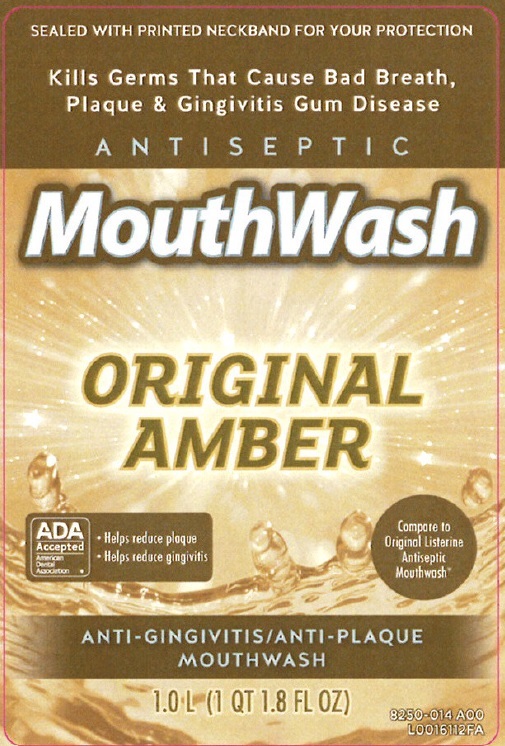 DRUG LABEL: Antiseptic Mouth Rinse
NDC: 71141-157 | Form: MOUTHWASH
Manufacturer: Lidl US, LLC
Category: otc | Type: HUMAN OTC DRUG LABEL
Date: 20260204

ACTIVE INGREDIENTS: EUCALYPTOL 0.92 mg/1 mL; MENTHOL 0.42 mg/1 mL; METHYL SALICYLATE 0.6 mg/1 mL; THYMOL 0.64 mg/1 mL
INACTIVE INGREDIENTS: WATER; ALCOHOL; BENZOIC ACID; POLOXAMER 407; SODIUM BENZOATE; CARAMEL

Dentalux_Lidl 318.003/318AH-AI
Antiseptic Mouthrinse

Active ingredients

Eucalyptol 0.092%

Menthol 0.042%

Methyl salicylate 0.060%

Thymol 0.064%

Purpose

Antigingivitis, Antiplaque

Use

helps control plaque that leads to gingivitis

Warnings

For this product

Do not use

If you have painful or swollen gums, pus from the gum line, loose teeth or increased spacing between the teeth. See your dentist immediately. These may be signs of periodontitis, a serious form of gum disease.

Stop use and ask a dentist if

gingivitis, bleeding, or redness persists for more than 2 weeks

Keep out of reach of children

If more than used for rinsing is accidentally swallowed, get medical help or contact a Poison Control Center right away.

Directions

adults and children 12 years of age and older - vigorously swish 20 mL (2/3 FL OZ or 4 teaspoonfuls) between teeth for 30 seconds then spit out; do not swallow

children under 12 years of age - consult a dentist or doctor

- This rinse is not intended to replace brushing or flossing

Other information

Cold weather may cloud this product. Its antiseptic properties are not affected. Store at room temperature (59°-77°F).

Inactive ingredients

water, alcohol 26.9%, benzoic acid, poloxamer 407, sodium benzoate, caramel

Questions or comments?

1-844-344-5071

*This product is not manufactued or distributed by Johnson & Johnson Corporation., owner of the registered trademark Listerine®.

DISTRIBUTED BY

Lidl US, LLC

Arlington, VA 22202

QUESTIONS?

1-844-344-5071

www.Lidl.com

LIDL

Love it! Guarantee

money refunded

item replaced

DSP-TN-21091 DSP-MO-20087

save water.lidl

Discard seal, empty & Replace Cap

Plastic bottle

how2recycle.info

Principal Panel Display

SEALED WITH PRINTED NECKBAND FOR YOUR PROTECTION

Kills Germs That Cause Bad Breath, Plaque, & Gingivitis Gum Disease

ANTISEPTIC

MOUTHWASH

ORIGINAL AMBER

ADA

ACCEPTED

American

Dental

Association

- Helps reduce plaque
- Helps reduce gingivitis

Compare to Original Listerine Antiseptic Mouthwash

ANTI-GINGIVITIS/ANTI-PLAQUE

MOUTHWASH

1.0 L (1 QT 1.8 FL OZ)

Principal Panel Display

dentalux

by LIDL®

ORIGINAL

ANTI-GINGIVITIS/ANTI-PLAQUE

MOUTHWASH

ANTISEPTIC

MOUTHWASH

ADA ACCEPTED

American Dental Association

- Helps prevent and redice plaque
- Helps prevent and redice gingivitis

SEALED WITH PRINTED NECKBAND FOR YOUR PROTECTION

Kills Germs that Cause Plaque, Gingivitis, Bad Breath

NDC 71141-157-12

50.7 FL OZ (1.58 QT) 1.5L